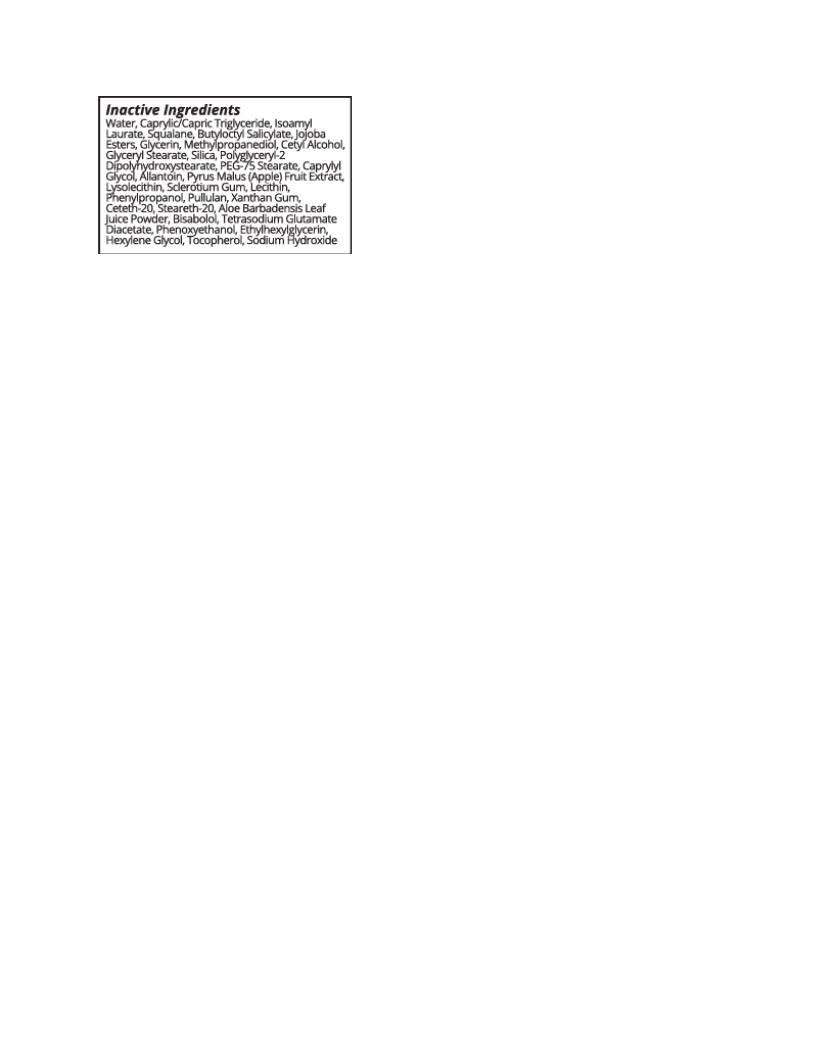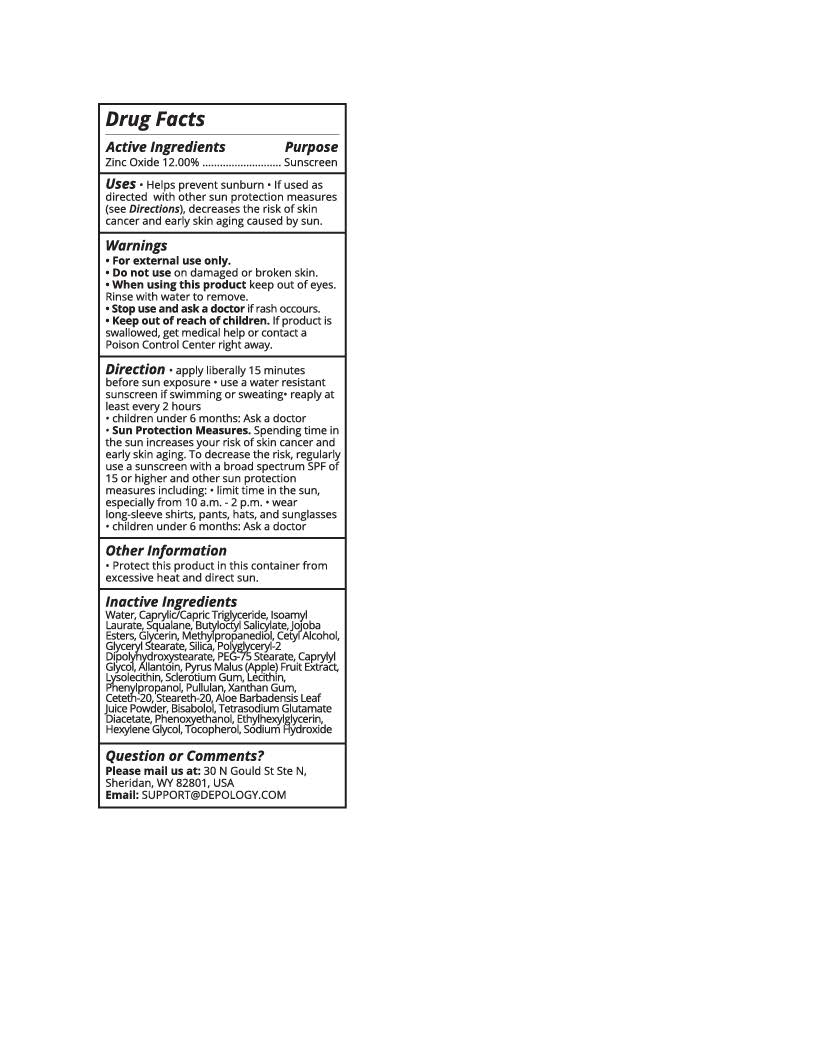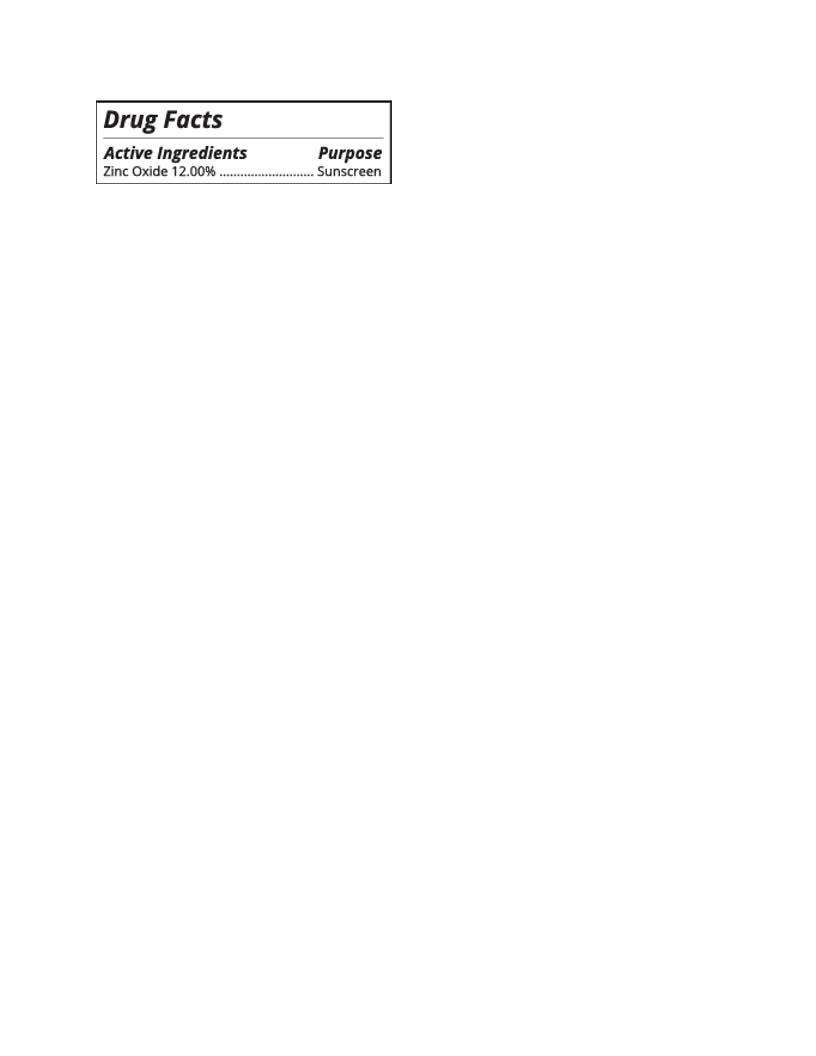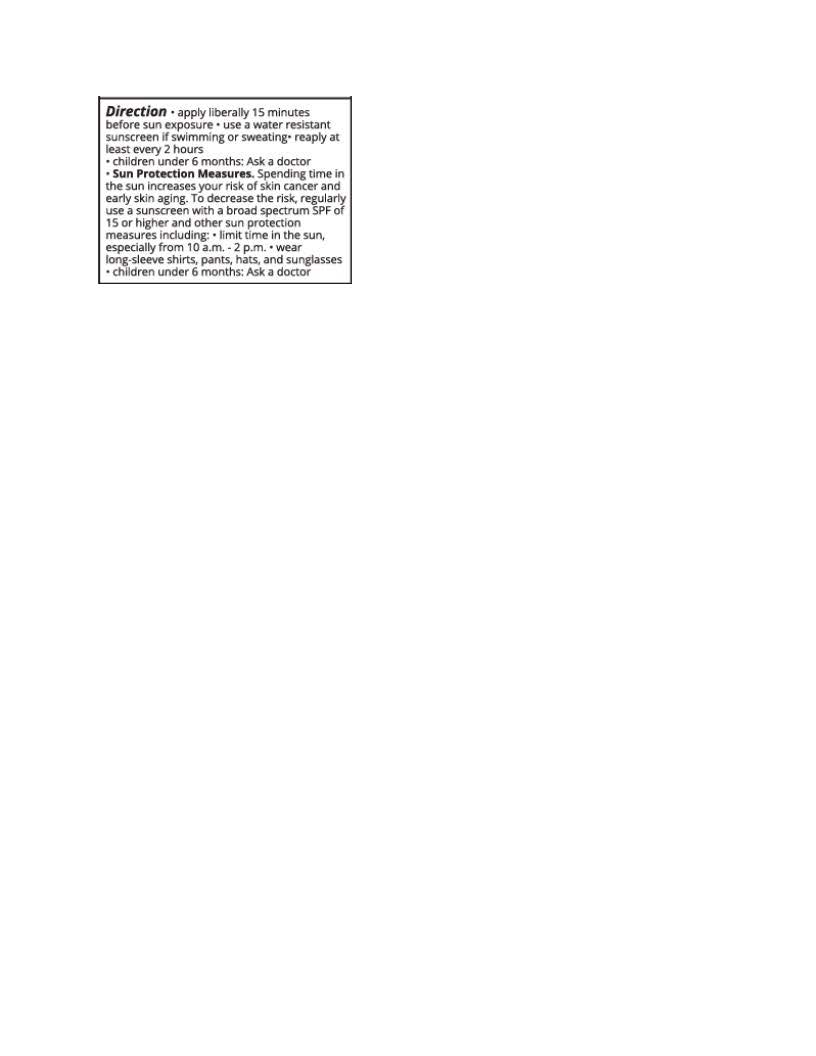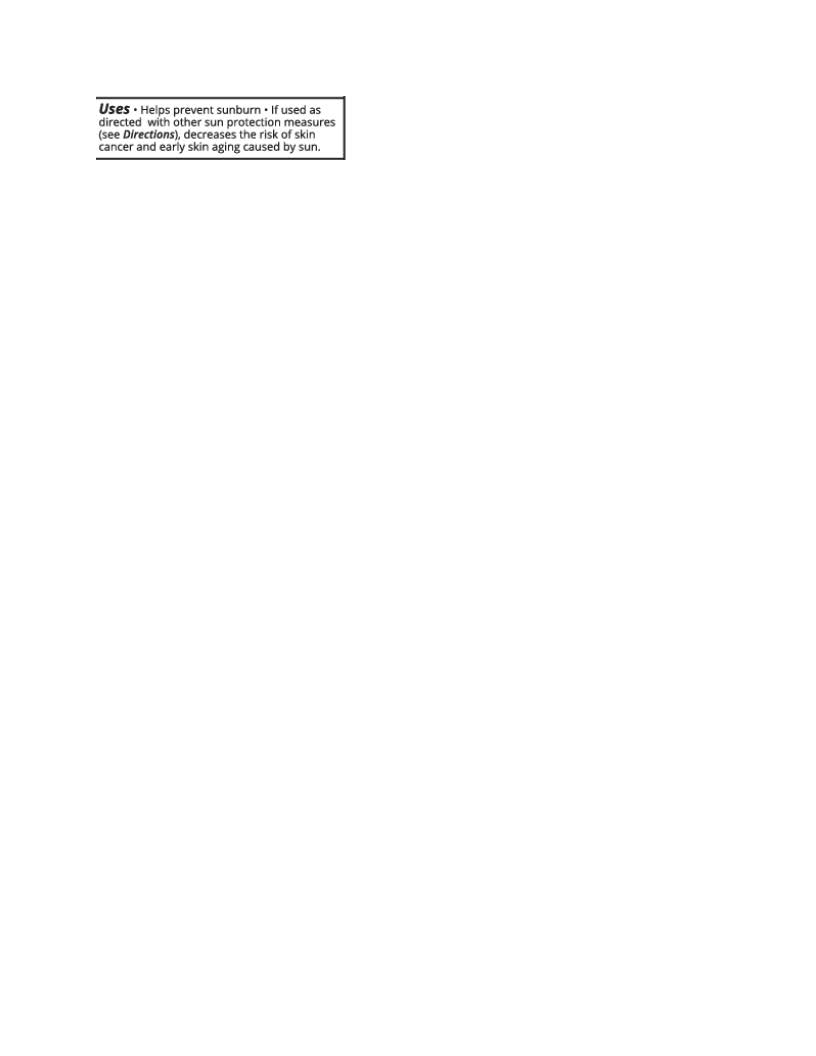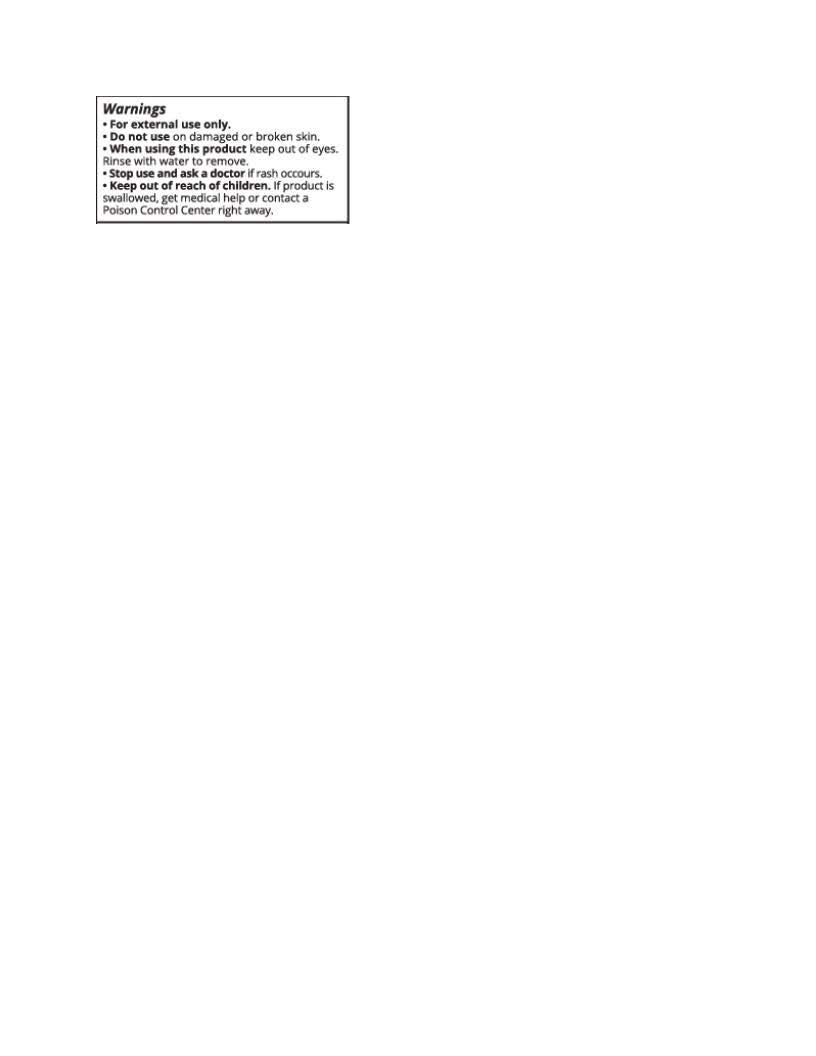 DRUG LABEL: Depology Essential Mineral UV Care
NDC: 84133-1039 | Form: LOTION
Manufacturer: Depology Holdings LLC
Category: otc | Type: HUMAN OTC DRUG LABEL
Date: 20251113

ACTIVE INGREDIENTS: ZINC OXIDE 132 mg/1 mL
INACTIVE INGREDIENTS: LECITHIN, SOYBEAN; POLYGLYCERYL-2 DIPOLYHYDROXYSTEARATE; HYDROLYZED JOJOBA ESTERS (ACID FORM); METHYLPROPANEDIOL; CAPRYLYL GLYCOL; PHENYLPROPANOL; XANTHAN GUM; ISOAMYL LAURATE; HEXYLENE GLYCOL; TOCOPHEROL; CETYL ALCOHOL; ETHYLHEXYLGLYCERIN; GLYCERIN; SILICON DIOXIDE; WATER; .ALPHA.-BISABOLOL, (+)-; BUTYLOCTYL SALICYLATE; CETETH-20; PULLULAN; SQUALANE; STEARETH-20; CYCLODEXTRINS

Depology Essential Mineral UV Care